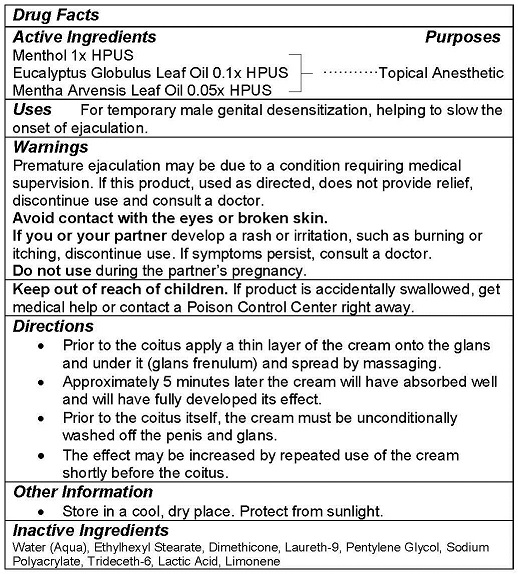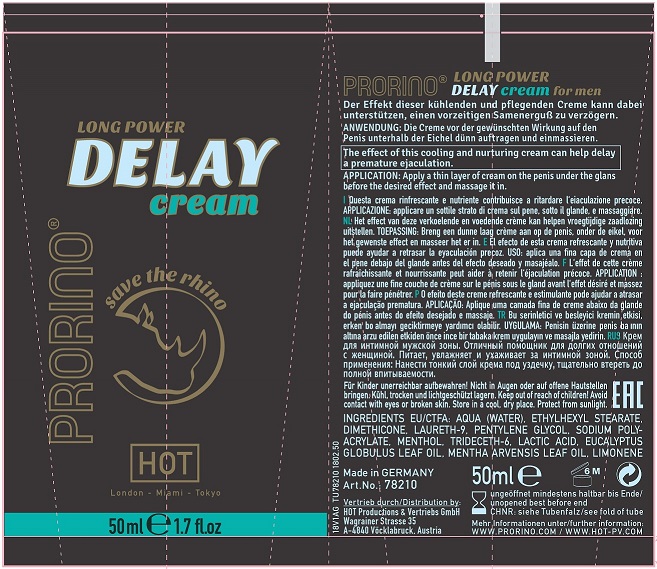 DRUG LABEL: PRORINO DELAY
NDC: 71326-102 | Form: CREAM
Manufacturer: HOT PRODUCTIONS AND VERTRIEBS GMBH
Category: homeopathic | Type: HUMAN OTC DRUG LABEL
Date: 20231005

ACTIVE INGREDIENTS: MENTHOL 1 g/100 mL; EUCALYPTUS OIL 0.097 g/100 mL; MENTHA ARVENSIS LEAF OIL 0.0478 g/100 mL
INACTIVE INGREDIENTS: WATER; ETHYLHEXYL STEARATE; DIMETHICONE; POLIDOCANOL; PENTYLENE GLYCOL; SODIUM POLYACRYLATE (8000 MW); TRIDECETH-6; LACTIC ACID; LIMONENE, (+/-)-

HOT PRODUCTS - Prorino Delay Cream (71326-102)

ACTIVE INGREDIENTS

Menthol 1x HPUS

Eucalyptus Globulus Leaf Oil 0.1X HPUS

Mentha Arvenses Leaf Oil 0.05x HPUS

PURPOSE

Topical Anesthetic

USE

For temporary male genital desensitization, helping to slow the onset of ejaculation.

WARNINGS

Premature ejaculation may be due to a condition requiring medical supervision. If this product, used as directed, does not provide relief, discontinue use and consult a doctor.
Avoid contact with the eyes or broken skin.
If you or your partner develop a rash or irritation, such as burning or itching, discontinue use. If symptoms persist, consult a doctor.
Do not use during the partner’s pregnancy.

Keep out of reach of children. If product is accidentally swallowed, get medical help or contact a Poison Control Center right away.

DIRECTIONS

- Prior to the coitus apply a thin layer of the cream onto the glans and under it (glans frenulum) and spread by massaging.
- Approximately 5 minutes later the cream will have absorbed well and will have fully developed its effect.
- Prior to the coitus itself, the cream must be unconditionally washed off the penis and glans.
- The effect may be increased by repeated use of the cream shortly before the coitus.

OTHER INFORMATION

- Store in a cool, dry place. Protect from sunlight.

INACTIVE INGREDIENTS

Water (Aqua), Ethylhexyl Stearate, Dimethicone, Laureth-9, Pentylene Glycol, Sodium Polyacrylate, Trideceth-6, Lactic Acid, Limonene